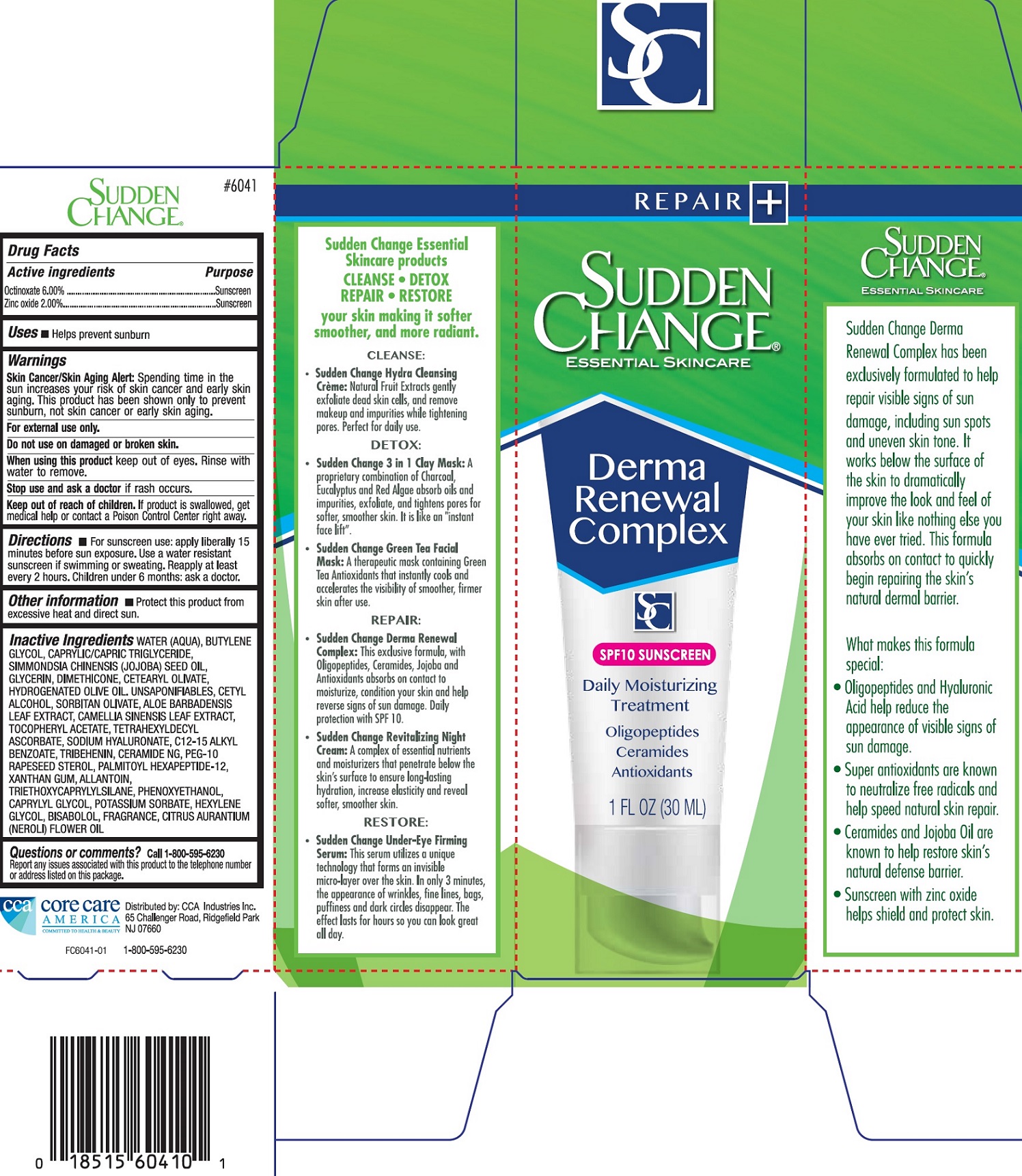 DRUG LABEL: Sudden Change Derma Renewal Complex
NDC: 61543-0003 | Form: CREAM
Manufacturer: CCA Industries Inc.
Category: otc | Type: HUMAN OTC DRUG LABEL
Date: 20210908

ACTIVE INGREDIENTS: OCTINOXATE 60 mg/1 mL; ZINC OXIDE 20 mg/1 mL
INACTIVE INGREDIENTS: WATER; BUTYLENE GLYCOL; MEDIUM-CHAIN TRIGLYCERIDES; GLYCERIN; DIMETHICONE; CETEARYL OLIVATE; HYDROGENATED OLIVE OIL; OLEA EUROPAEA (OLIVE) OIL UNSAPONIFIABLES; CETYL ALCOHOL; SORBITAN OLIVATE; ALOE VERA LEAF; GREEN TEA LEAF; .ALPHA.-TOCOPHEROL ACETATE; TETRAHEXYLDECYL ASCORBATE; HYALURONATE SODIUM; ALKYL (C12-15) BENZOATE; TRIBEHENIN; CERAMIDE NG; PEG-10 RAPESEED STEROL; PALMITOYL HEXAPEPTIDE-12; XANTHAN GUM; ALLANTOIN; TRIETHOXYCAPRYLYLSILANE; PHENOXYETHANOL; CAPRYLYL GLYCOL; POTASSIUM SORBATE; HEXYLENE GLYCOL; LEVOMENOL; CITRUS AURANTIUM FLOWER OIL

Sudden Change Derma Renewal Complex

Active Ingredient

Octinoxate 6.00%

Zinc oxide 2.00%

Purpose

Sunscreen

Uses:

Hepls prevent sunburn

Warnings

Skin Cancer/Skin Aging Alert: Spending time in the sun increases your risk of skin cancer and early skin aging. This product has been shown only to prevent sunburn, not skin cancer or early skin aging.

For external use only.

Do not use

on damaged or broken skin.

When using this product

keep out of eyes. Rinse with water to remove.

Stop use and ask a doctor

if rash occurs.

Keep out of the reach of children.

If product is swallowed, get medical help or contact a Poison Control Center right away.

Directions

- For sunsreen use: apply liberally 15 minutes before sun exposure. Use a water resistant sunscreen if swimming or sweating. Reapply at least every 2 hours. Children under 6 months: ask a doctor.

Other Information

- Protect this product from excessive heat and direct sun.

Inactive Ingredients

WATER (AQUA), BUTYLENE GLYCOL, CAPRYLIC/CAPRIC TRIGLYCERIDE, SIMMONDSIA, CHINENSIS (JOJOBA) SEED OIL, GLYCERIN, DIMETHICONE, CETEARYL OLIVATE, HYDROGENATED OLIVE OIL, UNSAPONIFIABLES, CETYL ALCOHOL, SORBITAN OLIVATE, ALOE BARBADENSIS LEAF EXTRACT, CAMELLIA SINENSIS LEAF EXTRACT, TOCOPHERYL ACETATE, TETRAHEXYLDECYL ASCORBATE, SODIUM HYALURONATE, C12-15 ALKYL BENZOATE, TRIBEHENIN, CERAMIDE NG, PEG-10 RAPESEED STEROL, PALMITOYL HEXAPEPTIDE-12, XANTHAN GUM, ALLANTOIN, TRIETHOXYCAPRYLYLSILANE, PHENOXYETHANOL, CAPRYLYL GLYCOL, POTASSIUM SORBATE, HEXYLENE GLYCOL, BISABOLOL, FRAGRANCE, CITRUS AURANTIUM (NEROLI) FLOWER OIL

Questions or Comments?

Call 1-800-595-6230

Report any issues associated with this product to the telephone number or address listed on this package.